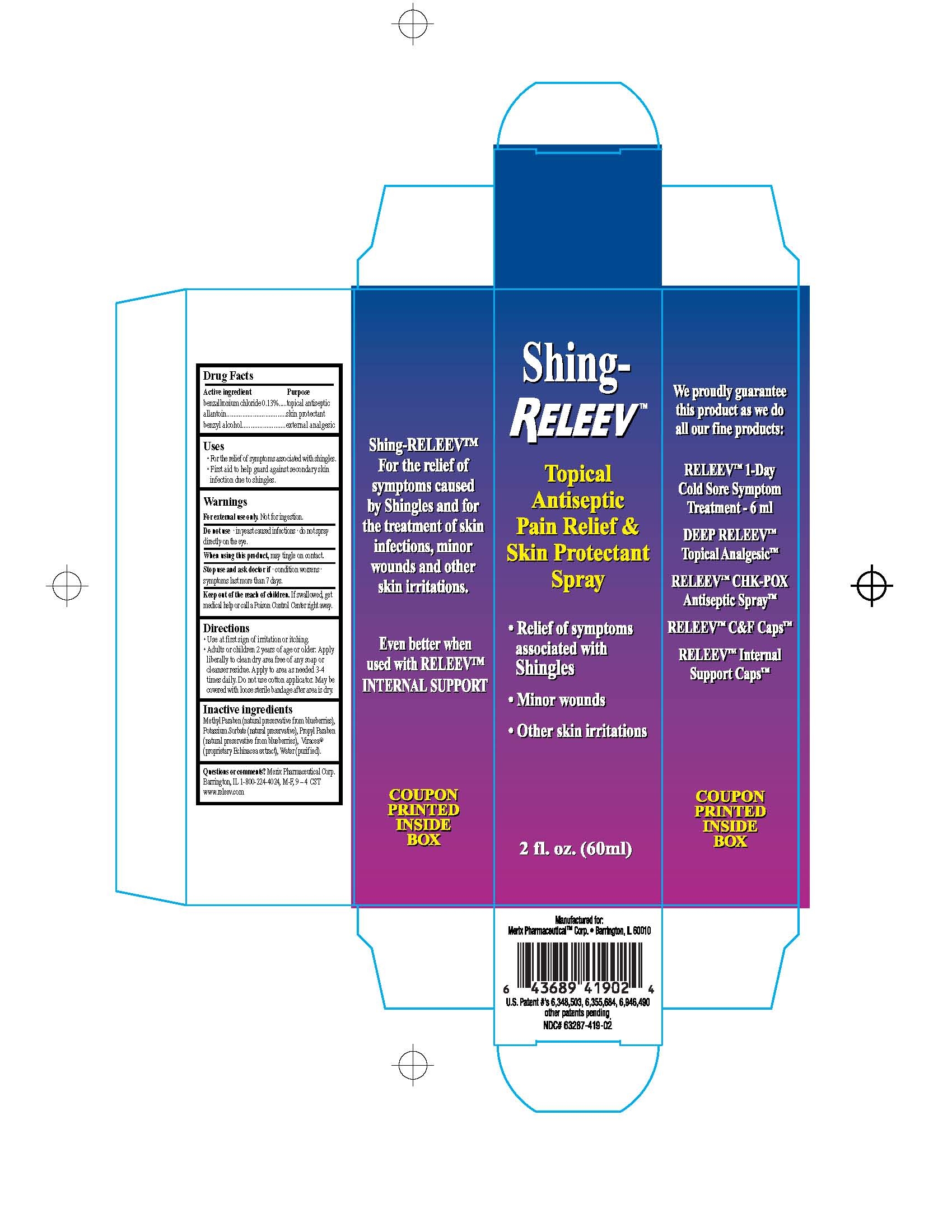 DRUG LABEL: shing-Releev 
NDC: 63287-420 | Form: LIQUID
Manufacturer: Merix Pharmaceutical Corp.
Category: otc | Type: HUMAN OTC DRUG LABEL
Date: 20120730

ACTIVE INGREDIENTS: Benzalkonium Chloride 1.3 mg/1 mL; Allantoin 5 mg/1 mL; Benzyl Alcohol 5 mg/1 mL
INACTIVE INGREDIENTS: Water; Methylparaben; Potassium Sorbate; Propylparaben; Echinacea purpurea flowering top

DRUGS FACTS

ACTIVE INGREDIENTS:

Benzalkanium Chloride .13%
Allantoin .5%
Benzyl Alcohol .5%

USES:

For the relive of symtoms associated with shingles including pain, Burning, Itching and tingling First aid to help guard against secondary skin infection due to shingles.

WARNINGS:

For external used only. Not for ingestion.

Do not used- in yeast infections- do not spray directly on the eyes

When using this product, may tingle on contact.

Stop used and ask doctor if - condition worsens- symptoms

last more then 7 days .

KEEP OUT OF REACH OF CHILDREN:

If swallowget medical help or contact a Poison Control Center right away.

DIRECTIONS:

Use at first sign of irritation or itching.
Adults and children 12 years or older. Clean without soap.
apply liberally to clean dry area free of soap or cleanser residue.

DOSAGE AND ADMINISTRATION

Apply to area as needed 3-4 times daily.
Do not use cotton applicator.
May be used with sterile bandage after area is dry.

Other Ingredients

.Methylparaben Potassium Sorbate (natural preservative).

Propylparaben , Viracea (proprietary Echinacea purpurea extract),

water (purified)

PACKAGE LABEL

Shing carton